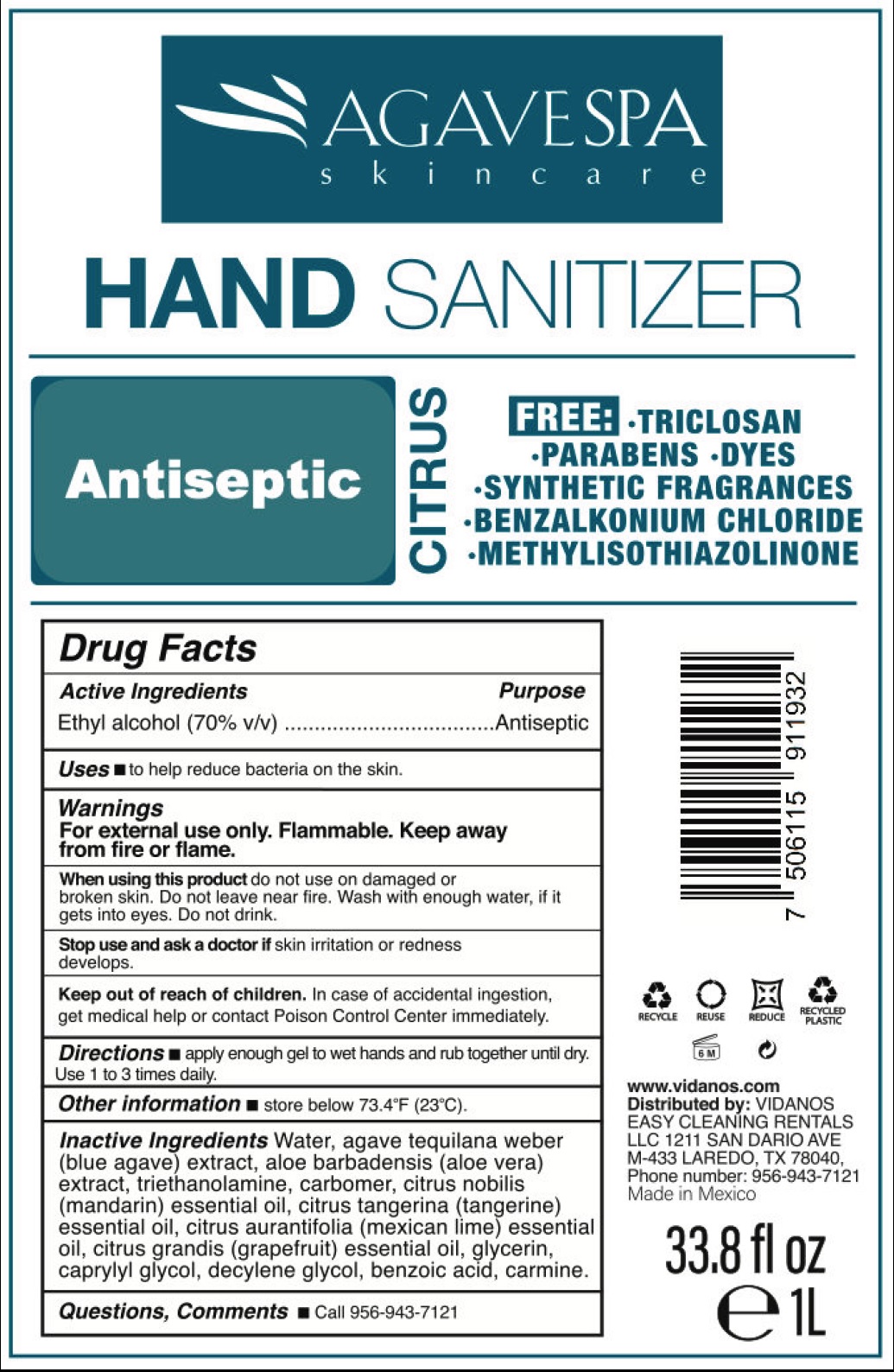 DRUG LABEL: HAND SANITIZER AGAVESPA SKINCARE
NDC: 77415-000 | Form: GEL
Manufacturer: DDI Multinacional, S.A. de C.V.
Category: otc | Type: HUMAN OTC DRUG LABEL
Date: 20200508

ACTIVE INGREDIENTS: ALCOHOL 0.7 mL/1 mL
INACTIVE INGREDIENTS: WATER; AGAVE TEQUILANA LEAF; ALOE VERA LEAF; TROLAMINE; CARBOMER HOMOPOLYMER, UNSPECIFIED TYPE; MANDARIN OIL; LIME OIL; GRAPEFRUIT OIL; GLYCERIN; CAPRYLYL GLYCOL; DECYLENE GLYCOL; BENZOIC ACID

HAND SANITIZER AGAVESPA SKINCARE

Active ingredients

Ethyl Alcohol (70% v/v)

Purpose

Antiseptic

Uses

- to help reduce bacteria on the skin.

Warnings

For external use only. Flammable. Keep away from fire or flame.

When using this product

do not use on damaged or broken skin. Do not leave near fire. Wash with enough water, if it gets into eyes. Do not drink.

Stop use and ask a doctor if

irritation and redness develops.

Keep out of reach of children.

In case of accidental ingestion, get medical help or contact a Poison Control Center immediately.

Directions

- apply enough gel to wet hands and rub together until dry. Use 1 to 3 times daily.

Other information

- store below 73.4oF (23oC)

Inactive Ingredients

Water, agave tequilana weber (blue agave) extract, aloe barbadensis (aloe vera) extract, aloe barbadensis (aloe vera) extract, triethanolamine, carbomer, citrus nobilis (mandarin) essential oil, citrus tangerina (tangerine) essential oil, citrus aurantifolia (mexica lime) essential oil, citrus grandis (grapefruit) essential oil, glycerin, caprylys glycol, decylene glycol, benzoic acid, carmine.

Questions, Comments

- Call 956-943-7121